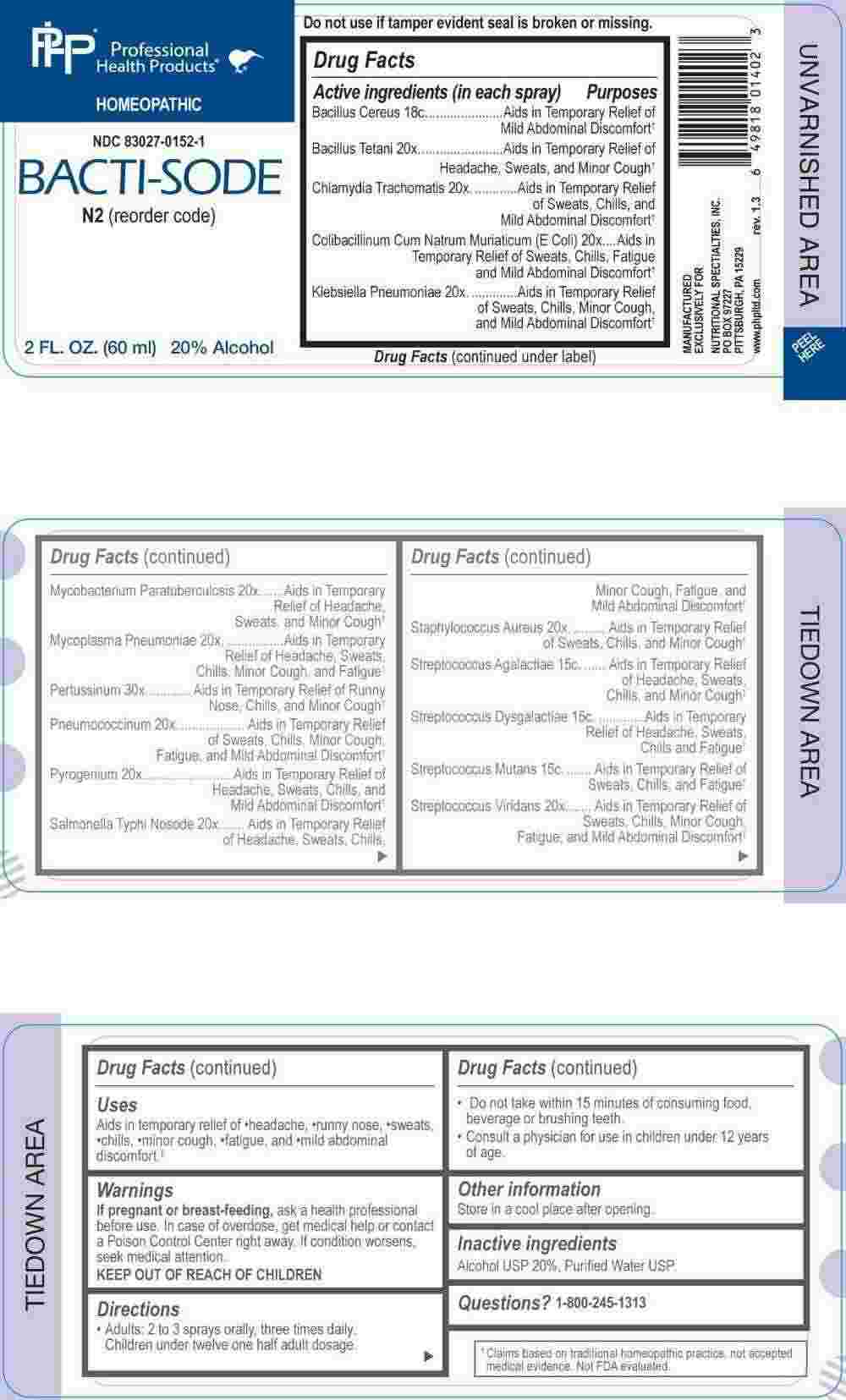 DRUG LABEL: Bacti Sode
NDC: 83027-0152 | Form: SPRAY
Manufacturer: Nutritional Specialties, Inc.
Category: homeopathic | Type: HUMAN OTC DRUG LABEL
Date: 20250429

ACTIVE INGREDIENTS: CLOSTRIDIUM TETANI 20 [hp_X]/1 mL; CHLAMYDIA TRACHOMATIS 20 [hp_X]/1 mL; ESCHERICHIA COLI 20 [hp_X]/1 mL; KLEBSIELLA PNEUMONIAE 20 [hp_X]/1 mL; MYCOBACTERIUM AVIUM SUBSP. PARATUBERCULOSIS 20 [hp_X]/1 mL; MYCOPLASMA PNEUMONIAE 20 [hp_X]/1 mL; STREPTOCOCCUS PNEUMONIAE 20 [hp_X]/1 mL; SALMONELLA ENTERICA ENTERICA SEROVAR TYPHI 20 [hp_X]/1 mL; STAPHYLOCOCCUS AUREUS 20 [hp_X]/1 mL; STREPTOCOCCUS VIRIDANS GROUP 20 [hp_X]/1 mL; RANCID BEEF 20 [hp_X]/1 mL; HUMAN SPUTUM, BORDETELLA PERTUSSIS INFECTED 30 [hp_X]/1 mL; STREPTOCOCCUS AGALACTIAE 15 [hp_C]/1 mL; STREPTOCOCCUS DYSGALACTIAE 15 [hp_C]/1 mL; STREPTOCOCCUS MUTANS 15 [hp_C]/1 mL; BACILLUS CEREUS 18 [hp_C]/1 mL
INACTIVE INGREDIENTS: WATER; ALCOHOL

DRUG FACTS:

ACTIVE INGREDIENTS:

(in each spray) Bacillus Cereus 18C, Bacillus Tetani 20X, Chlamydia Trachomatis 20X, Colibacillinum Cum Natrum Muriaticum 20X, Klebsiella Pneumoniae 20X, Mycobacterium Paratuberculosis 20X, Mycoplasma Pneumoniae 20X, Pertussinum 30X, Pneumococcinum 20X, Pyrogenium 20X, Salmonella Typhi Nosode 20X, Staphylococcus Aureus 20X, Streptococcus Agalactiae 15C, Streptococcus Dysgalactiae 15C, Streptococcus Mutans 15C, Streptococcus Viridans 20X.

PURPOSE:

Bacillus Cereus – Aids in Temporary Relief of Mild Abdominal Discomfort,† Bacillus Tetani – Aids in Temporary Relief of Headache, Sweats, and Minor Cough,† Chlamydia Trachomatis – Aids in Temporary Relief of Sweats, Chills, and Mild Abdominal Discomfort,† Colibacillinum Cum Natrum Muriaticum – Aids in Temporary Relief of Sweats, Chills, Fatigue and Mild Abdominal Discomfort,† Klebsiella Pneumoniae – Aids in Temporary Relief of Sweats, Chills, Minor Cough, and Mild Abdominal Discomfort,† Mycobacterium Paratuberculosis – Aids in Temporary Relief of Headache, Sweats, and Minor Cough,† Mycoplasma Pneumoniae – Aids in Temporary Relief of Headache, Sweats, Chills, Minor Cough, and Fatigue,† Pertussinum – Aids in Temporary Relief of Runny Nose, Chills, and Minor Cough,† Pneumococcinum – Aids in Temporary Relief of Sweats, Chills, Minor Cough, Fatigue, and Mild Abdominal Discomfort,† Pyrogenium – Aids in Temporary Relief of Headache, Sweats, Chills, and Mild Abdominal Discomfort,† Salmonella Typhi Nosode – Aids in Temporary Relief of Headache, Sweats, Chills, Minor Cough, Fatigue, and Mild Abdominal Discomfort,† Staphylococcus Aureus – Aids in Temporary Relief of Sweats, Chills, and Minor Cough,† Streptococcus Agalactiae – Aids in Temporary Relief of Headache, Sweats, Chills, and Minor Cough,† Streptococcus Dysgalactiae – Aids in Temporary Relief of Headache, Sweats, Chills, and Fatigue,† Streptococcus Mutans – Aids in Temporary Relief of Sweats, Chills, and Fatigue,† Streptococcus Viridans – Aids in Temporary Relief of Sweats, Chills, Minor Cough, Fatigue, and Mild Abdominal Discomfort†

†Claims based on traditional homeopathic practice, not accepted medical evidence. Not FDA evaluated.

USES:

Aids in temporary relief of •headache, •runny nose, •sweats, chills, minor cough, fatigue, and mild abdominal discomfort.†

†Claims based on traditional homeopathic practice, not accepted medical evidence. Not FDA evaluated.

WARNINGS:

If pregnant or breast-feeding, ask a health professional before use.

In case of overdose, get medical help or contact a Poison Control Center right away.

If condition worsens, seek medical attention.

KEEP OUT OF REACH OF CHILDREN

Do not use if tamper evident seal is broken or missing.

Store in a cool place after opening

KEEP OUT OF REACH OF CHILDREN:

In case of overdose, get medical help or contact a Poison Control Center right away.

DIRECTIONS:

• Adults: 2 to 3 sprays orally, three times daily. Children under twelve one half adult dosage.

• Do not take within 15 minutes of consuming food, beverage or brushing teeth.

Consult a physician for use in children under 12 years of age.

INACTIVE INGREDIENTS:

Alcohol USP 20%, Purified Water USP.

QUESTIONS:

MANUFACTURED EXCLUSIVELY FOR

NUTRITIONAL SPECIALTIES, INC.

PO BOX 97227

PITTSBURG, PA 15229

www.phpltd.com

1-800-245-1313

PACKAGE LABEL DISPLAY:

Professional

Health Products

HOMEOPATHIC

NDC 83027-0152-1

BACTI-SODE

2 FL. OZ (60 ml)